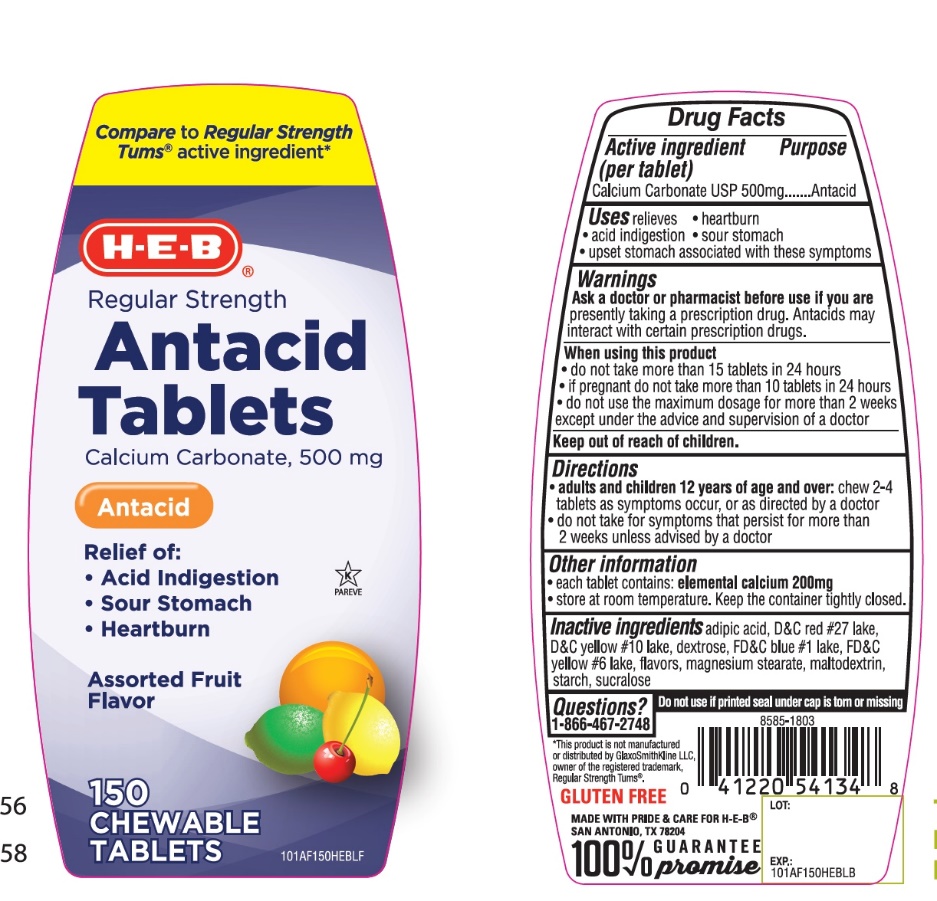 DRUG LABEL: HEB Regular strength

NDC: 37808-101 | Form: TABLET, CHEWABLE
Manufacturer: HEB
Category: otc | Type: HUMAN OTC DRUG LABEL
Date: 20251003

ACTIVE INGREDIENTS: CALCIUM CARBONATE 500 mg/1 1
INACTIVE INGREDIENTS: ADIPIC ACID; D&C RED NO. 27; D&C YELLOW NO. 10; DEXTROSE, UNSPECIFIED FORM; FD&C BLUE NO. 1; FD&C YELLOW NO. 6; MAGNESIUM STEARATE; MALTODEXTRIN; STARCH, CORN; SUCRALOSE

HEB Regular Strength Assorted Fruit Antacid Tablets

Active ingredient (per tablet)

Calcium Carbonate USP 500mg

Purpose

Antacid

Uses

relieves

• heartburn

• acid indigestion

• sour stomach

• upset stomach associated with these symptoms

Warnings

Ask a doctor or pharmacist before use if you arepresently taking a prescription drug. Antacids may interact with certain prescription drugs.

When using this product

- do not take more than 15 tablets in 24 hours
- If pregnant do not take more than10 tablets in 24 hours
- do not use the maximum dosage for more than 2 weeks except under the advice and supervision of a doctor.

Directions

- adults and children 12 years and over: chew 2-4 tablets as symptoms occur, or as directed by a doctor
- do not take for symptoms that persist for more than 2 weeks unless advised by a doctor.

Other information

• each tablet contains:elemental calcium 200 mg

• store at room temperature. Keep the container tightly closed.

Inactive ingredients

adipic acid, D&C Red No. 27, D&C Yellow No. 10, dextrose, FD&C Blue No. 1, FD & C Yellow No. 6, flavors, magnesium stearate, maltodextrin, starch, sucralose.

Questions or comments?

1-866-467-2748

DO NOT USE IF PRINTED SEAL UNDER CAP IS TORN OR MISSING.

Package/Label Principal Display Panel

NDC 37808-101-16

HEB®

Compare to Regular Strength Tum®active ingredient*

REGULAR STRENGTH

Antacid Tablets

CALCIUM CARBONATE 500 mg/Antacid

Relief of:

- Acid Indigestion
- Sour Stomach
- Heartburn

ASSORTED FRUIT FLAVORS

150 CHEWABLE TABLETS

GLUTEN-FREE

K PAREVE

MADE WITH PRIDE & CARE FOR H-E-B® SAN ANTONIA, TX 78204

100% GUARANTEE promise

*This product is not manufactured or distributed by GlaxoSmithKline LLC, the owner of the registered trademark, Regular Strength Tums®.